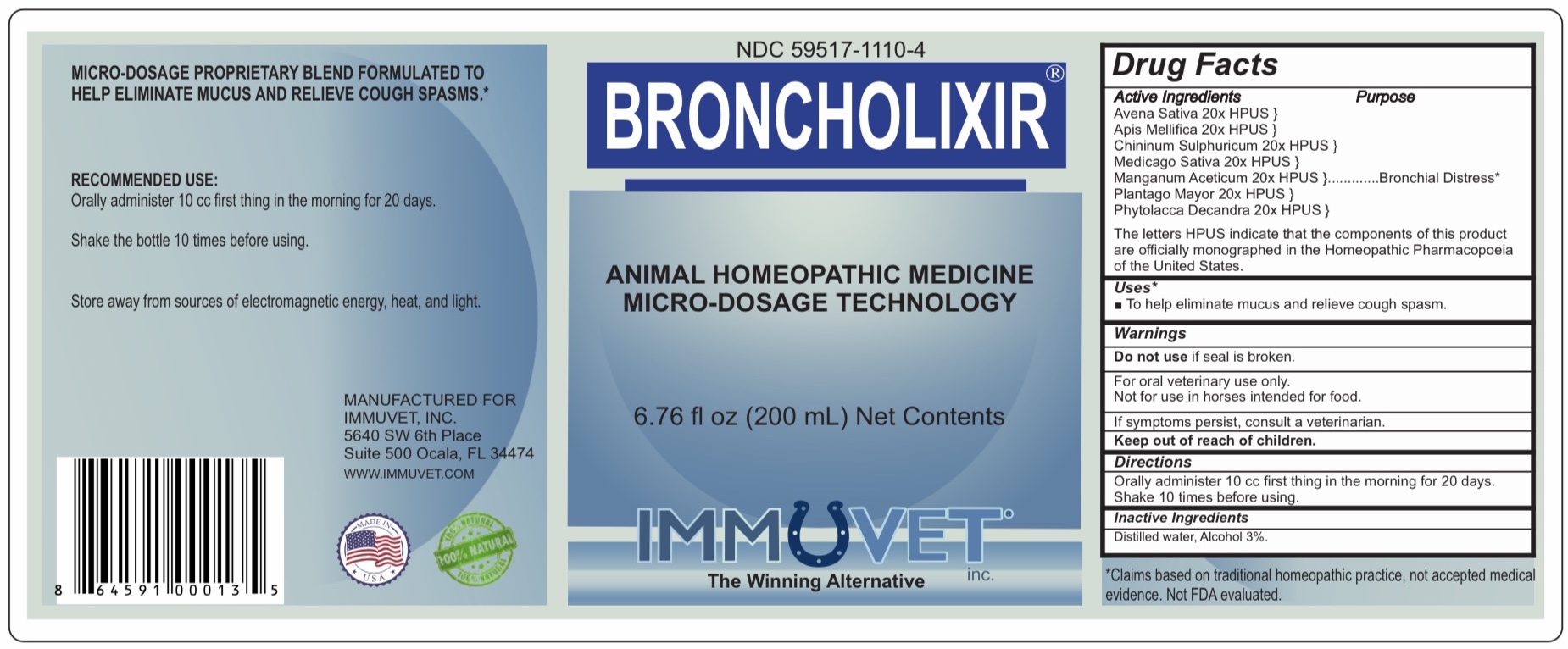 DRUG LABEL: BRONCHOLIXIR
NDC: 59517-1110 | Form: LIQUID
Manufacturer: Immuvet, Inc.
Category: homeopathic | Type: OTC ANIMAL DRUG LABEL
Date: 20251104

ACTIVE INGREDIENTS: PLANTAGO MAJOR 20 [hp_X]/1 mL; QUININE SULFATE 20 [hp_X]/1 mL; AVENA SATIVA WHOLE 20 [hp_X]/1 mL; MEDICAGO SATIVA WHOLE 20 [hp_X]/1 mL; APIS MELLIFERA 20 [hp_X]/1 mL; MANGANESE ACETATE TETRAHYDRATE 20 [hp_X]/1 mL; PHYTOLACCA AMERICANA ROOT 20 [hp_X]/1 mL
INACTIVE INGREDIENTS: ALCOHOL; WATER

Broncholixir

PURPOSE

To increase the rate of removal of mucus and relieve cough spasms associated with chronic equine productive lung conditions*

DIRECTIONS

Administer orally 10cc first thing in the morning for 20 days. Shake 10 times before using.

ACTIVE INGREDIENTS

Avena Sativa 20x
Medicago 20x
Apis Melifica 20x
Chininum Sulphuricum 20x
Manganum 20x
Phytolaca Decandra 20x
Plantago Major 20x

INACTIVE INGREDIENTS

Distilled water, Alcohol 5%

WARNINGS

Do not use if seal is broken.
For Oral Veterinary Use Only.
Not for use in Horses intended for food.
If problems persist, contact a veterinarian.
Keep out of reach of children.

OTHER INFORMATION

*Claims based on traditional homeopathic practice, not accepted medical evidence. Not FDA evaluated